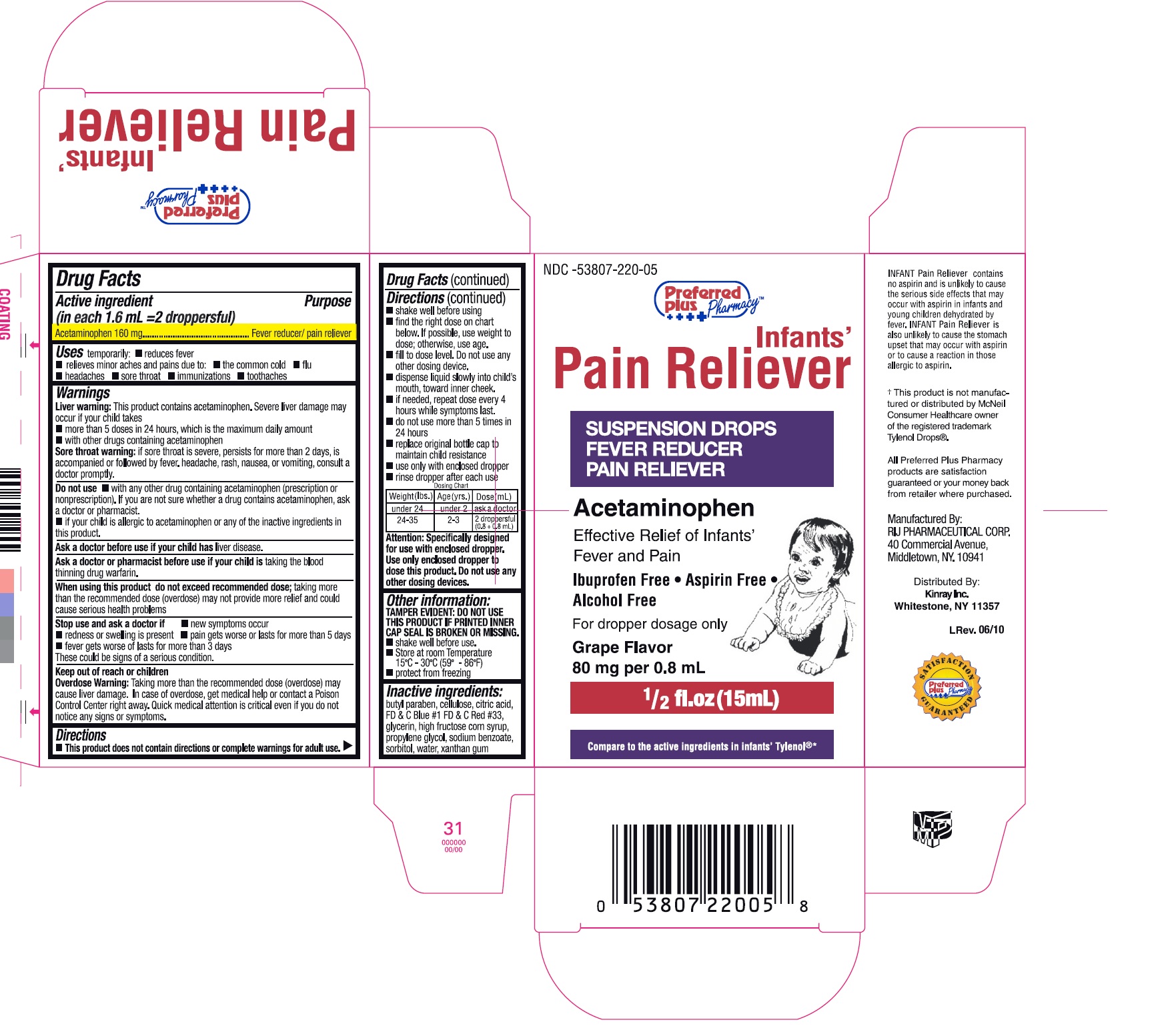 DRUG LABEL: Infants Pain Reliever
NDC: 53807-220 | Form: SUSPENSION
Manufacturer: Rij Pharmaceutical Corporation
Category: otc | Type: HUMAN OTC DRUG LABEL
Date: 20180502

ACTIVE INGREDIENTS: Acetaminophen 160 mg/1.6 mL
INACTIVE INGREDIENTS: BUTYLPARABEN; POWDERED CELLULOSE; CITRIC ACID MONOHYDRATE; D&C RED NO. 33; FD&C BLUE NO. 1; GLYCERIN; HIGH FRUCTOSE CORN SYRUP; PROPYLENE GLYCOL; SODIUM BENZOATE; SODIUM CITRATE; XANTHAN GUM; SORBITOL; WATER

Drug Facts

Active ingredient (in each 1.6 mL = 2 droppersful)

Acetaminophen 160 mg

Purpose

Fever reducer/ pain reliever

Uses

temporarily:

- reduces fever
- relieves minor aches and pains due to:
  - the common cold
  - flu
  - headache
  - sore throat
  - immunizations
  - toothache

Warnings

Liver warning:

This product contains acetaminophen.

Severe liver damage may occur if your child takes

- more than 5 doses in 24 hours, which is the maximum daily amount
- with other drugs containing acetaminophen

Sore throat warning

if sore throat is severe, persists for more than 2 days, is accompanied or followed by fever, headache, rash, nausea, or vomiting, consult a doctor promptly.

Do not use

- with any other drug containing acetaminophen (prescription or nonprescription). If you are not sure whether a drug contains acetaminophen, ask a doctor or pharmacist.
- if your child is allergic to acetaminophen or any of the inactive ingredients in this product

Ask a doctor before use if your child has liver disease

Ask a doctor or pharmacist before use if your child is taking the blood thinning drug warfarin

When using this product do not exceed recommended dose; taking more than the recommended dose (overdose) may not provide more relief and could cause serious health problems

Stop use and ask a doctor if

- new symptoms occur
- redness or swelling is present
- pain gets worse or lasts more than 5 days
- fever gets worse or lasts more than 3 days

These could be signs of a serious condition.

Keep out of reach of children.

Overdose warning

Taking more than the recommended dose (overdose) may cause liver damage. In case of overdose, get medical help or contact a Poison Control Center right away. Quick medical attention is critical even if you do not notice any signs or symptoms.

Directions

- This product does not contain directions or complete warnings for adult use.
- shake well before using
- find right dose on chart below. If possible, use weight to dose; otherwise, use age.
- fill to dose level. Do not use any other dosing device.
- dispense liquid slowly into child's mouth, toward inner cheek.
- if needed, repeat dose every 4 hours while symptoms last.
- do not give use than 5 times in 24 hours
- replace original bottle cap to maintain child resistance
- use only with enclosed dropper
- rinse dropper after each use

Dosing Chart

Weight (lbs.) | Age (yrs.) | Dose (mL)
under 24 | under 2 | ask a doctor
24-35 | 2-3 | 2 droppersful (0.8 + 0.8 mL)

Attention: Specifically designed for use with enclosed dropper. Use only enclosed dropper to dose this product. Do not use any other dosing devices.

Other information

- TAMPER EVIDENT: DO NOT USE THIS PRODUCT IF PRINTED INNER CAP SEAL IS BROKEN OR MISSING
- shake well before use.
- Store at room Temperature 15º - 30ºC (59º - 86ºF)
- protect from freezing.

Inactive ingredients

butyl paraben, cellulose, citric acid, FD&C Blue # 1 FD&C Red # 33, glycerin, high fructose corn syrup, propylene glycol, sodium benzoate, sorbitol, water, xanthan gum